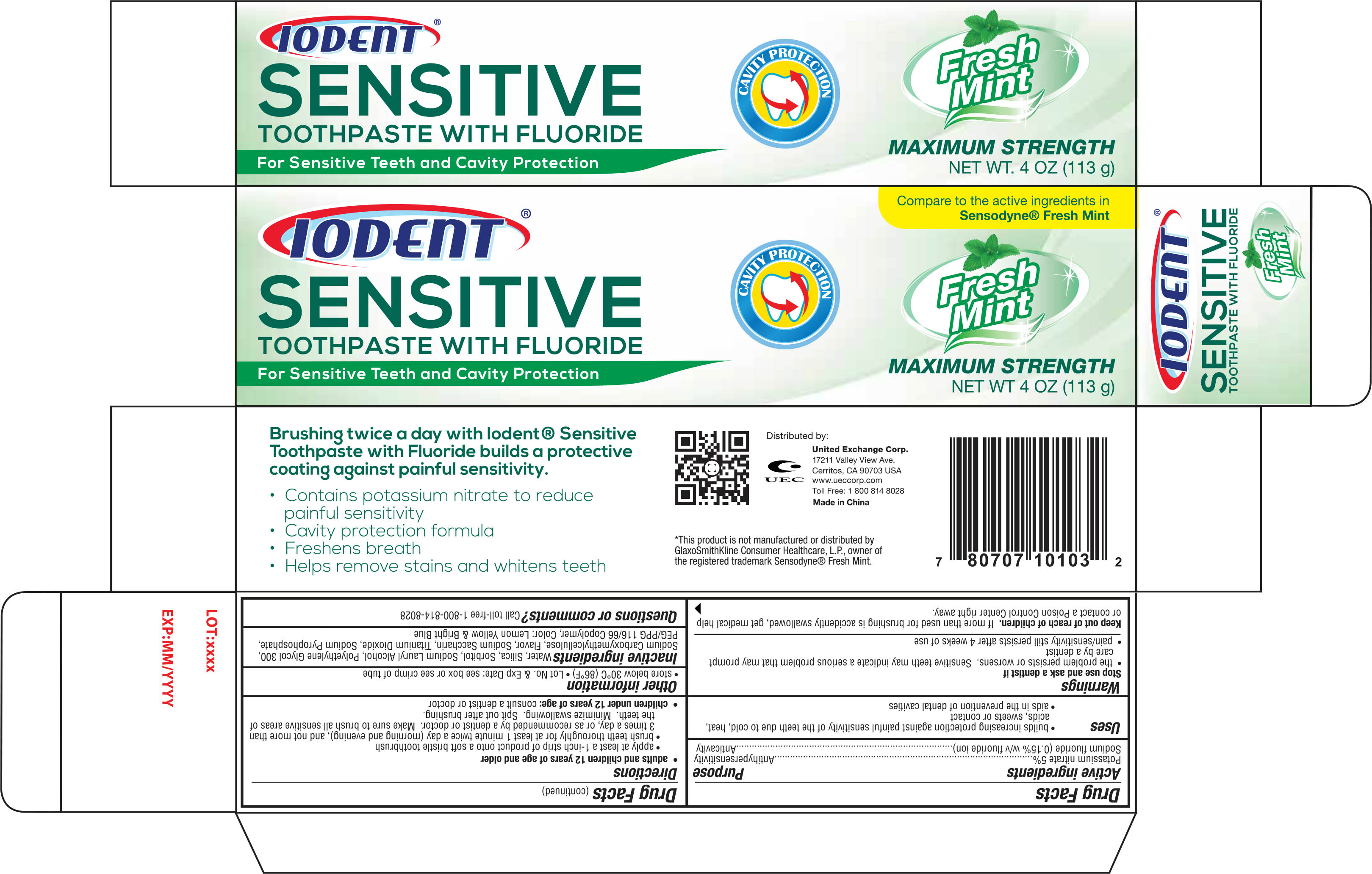 DRUG LABEL: Iodent Sensitive Fresh Mint
NDC: 65923-101 | Form: PASTE
Manufacturer: United Exchange Corp.
Category: otc | Type: HUMAN OTC DRUG LABEL
Date: 20161221

ACTIVE INGREDIENTS: POTASSIUM NITRATE 5 mg/100 g; SODIUM FLUORIDE .15 mg/100 g
INACTIVE INGREDIENTS: SORBITOL; HYDRATED SILICA; WATER; POLYETHYLENE GLYCOL 300; CARBOXYMETHYLCELLULOSE SODIUM; SACCHARIN SODIUM; TITANIUM DIOXIDE; SODIUM PYROPHOSPHATE; PEG/PPG-116/66 COPOLYMER

Active ingredients Purpose

Potassium nitrate 5%--------------------------------------------------- Antihypersensitivity

Sodium fluoride (0.15% w/v fluoride ion)------------------------------Anticavity

Uses

- Builds increasing protection against painful sensitivity of the teeth due to cold, heat, acids, sweets or contact
- aids in the prevention of dental cavities

Warnings

Stop use and ask a dentist if

- the problem persists or worsens. Sensitivie teeth may indicate a serious problem that may prompt care by a dentist
- pain/sensitivity still persists after 4 weeks of use

Keep out of reach of children.

If more than used for brushing is accidently swallowed, get medical help or contact a Poison Control Center right away.

Directions

adults and children 12 years of age and older

- apply at least a 1-inch strip of product onto a soft bristle toothbruch
- brush teeth thoroughly for at least 1 minute twice a day (morning and evening), and not more than 3 times a day, or as recommende by a dentist or doctor. Make sure to brush all sensitive areas of the teeth. Minimize swallowing. Spit out after brushing.

children under 12 years of age:consult a dentist or doctor

Other Information

- store below 40°C (86°F)
- Lot No & Exp Date:see box or see crimp of tube

Inactive ingredients

Water, Silica, Sorbitol, Sodium Lauryl Alcohol, Polyethylene Glycol 300, Sodium Carboxymethylcellulose, Floavor, Sodium Sacchrin, Titanium Dioxide, Sodium Pyrophosphate, PEG/PPG 116/66 Copolymer, Color: Lemon Yellow & Bright Blue

DOSAGE AND ADMINISTRATION

Distributed by:

United Exchange Corp.

17211 Valley View Ave.

Cerritos, CA 90703 USA